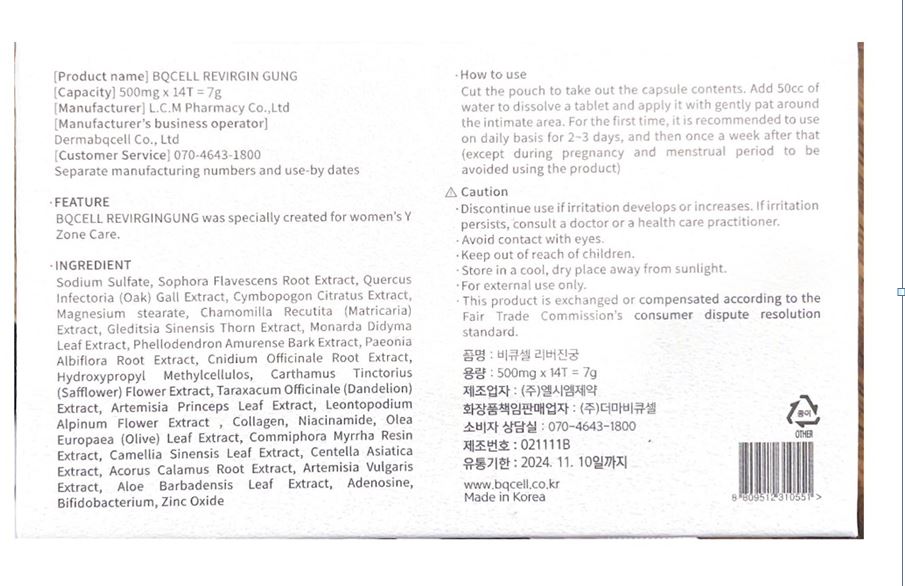 DRUG LABEL: BQCELL REVIRGIN GUNG
NDC: 82665-0001 | Form: TABLET
Manufacturer: Dermabqcell Co., Ltd.
Category: otc | Type: HUMAN OTC DRUG LABEL
Date: 20220408

ACTIVE INGREDIENTS: SODIUM SULFATE 0.235 g/1 1
INACTIVE INGREDIENTS: NIACINAMIDE; ADENOSINE

ACTIVE INGREDIENT

sodium fulfate

INACTIVE INGREDIENT

Collagen
Niacinamide
Olea Europaea (Olive) Leaf Extract
Commiphora Myrrha Resin Extract
Lactobacillus
Adenosine
Magnesium stearate
Leontopodium Alpinum Flower Extract
Sophora Flavescens Root Extract
Quercus Infectoria (Oak) Gall Extract
Cymbopogon Citratus Extract
Chamomilla Recutita (Matricaria) Extract
Gleditsia Australis Thorn Extract
Monarda Didyma Leaf Extract
Phellodendron Amurense Bark Extract
Paeonia Albiflora Root Extract
Cnidium Officinale Root Extract
Hydroxypropyl Methylcellulose
Carthamus Tinctorius (Safflower) Flower Extract
Taraxacum Officinale (Dandelion) Extract
Artemisia Princeps Leaf Extract
Camellia Sinensis Leaf Extract
Centella Asiatica Extract
Acorus Calamus Root Extract
Artemisia Vulgaris Extract
Aloe Barbadensis Leaf Extract
Bifidobacterium
Zinc Oxide

PURPOSE

feminine cleanser

Keep out of reach of children

INDICATIONS AND USAGE

1. Cut the pouch and take out the pill-like contents.
2. Dissolve 1 pill in 50cc of water and use it as if massaging around the vulva.
3. When using it for the first time, it is recommended to use it every day for 2-3 days. After that, it is recommended to use once a week on average (except during pregnancy and menstrual period)
4. The effect is better if you learn the proper usage and cycle according to individual differences.

WARNINGS

- external use only

- Be careful not to swallow

DOSAGE AND ADMINISTRATION

For external use only